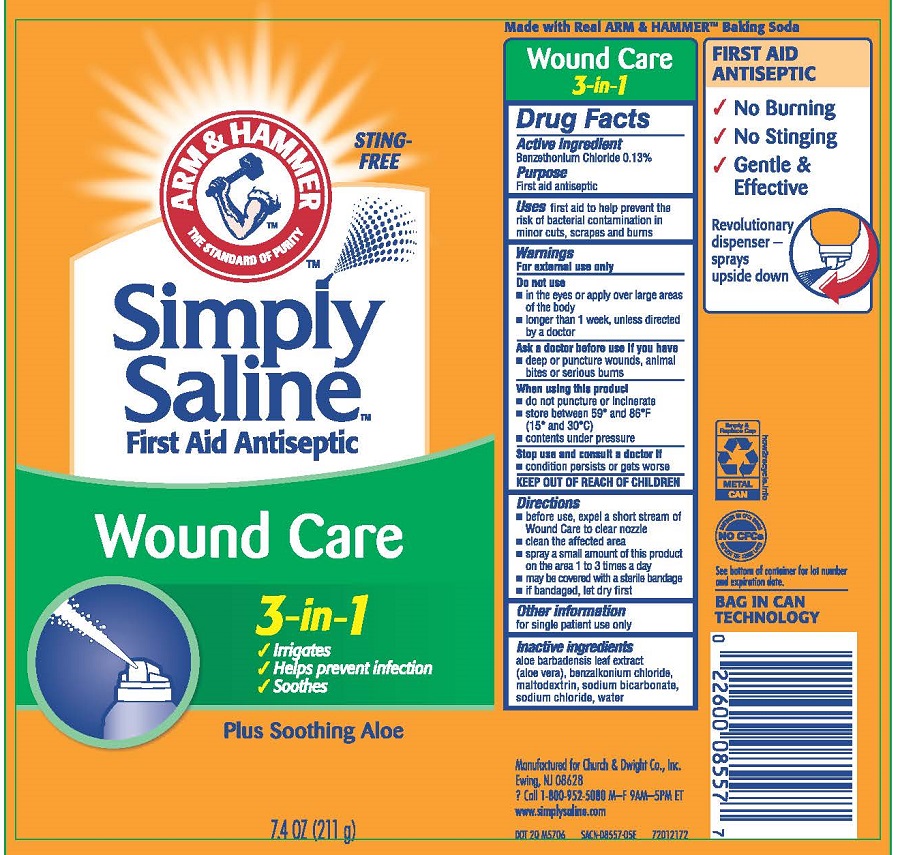 DRUG LABEL: Simply Saline
NDC: 10237-700 | Form: SPRAY
Manufacturer: Church & Dwight Co., Inc.
Category: otc | Type: HUMAN OTC DRUG LABEL
Date: 20250601

ACTIVE INGREDIENTS: BENZETHONIUM CHLORIDE 1 mg/13 mL
INACTIVE INGREDIENTS: ALOE VERA LEAF; BENZALKONIUM CHLORIDE; MALTODEXTRIN; WATER; SODIUM BICARBONATE; SODIUM CHLORIDE

Simply Saline 3 in 1 Wound Care

Wound Care 3 in 1 Active ingredients

Benzethonium Chloride 0.13%

Purpose

First aid Antiseptic

Uses

First aid to help prevent the risk of bacterial contamination in minor cuts, scrapes and burns.

Warnings For external use only.

Do not use

- in the eyes or apply over large areas of the body
- longer that 1 week, unless directed by a doctor

Ask a doctor before use if you have

- deep or puncture wounds, animal bites or serious burns

When using this product

- do not puncture or incinerate
- store between 59 and 86F (15 and 30C)
- contents under pressure

Stop use and consult a doctor if

- condition persists or gets worse

KEEP OUT OF REACH OF CHILDREN.

Directions

- before use, expel a short stream of Wound Care to clear nozzle
- clean the affected area
- spray a small amount of this product on the area 1 to 3 times a day
- may be covered with a sterile bandage
- if bandaged, let dry first

Other information

for single patient use only

Inactive ingredients

aloe barbadensis leaf extract (aloe vera), benzalkonium chloride, maltodextrin, purified water, sodium bicarbonate, sodium chloride

Product Image

Sting Free

Arm and Hammer

The standard of Purity

Simply Saline

First Aid Antiseptic

Wound Care

3 in 1

Irrigates

Helps prevent infections

Soothes

Plus Soothing Aloe

7.4 OZ (211 mL)

Image